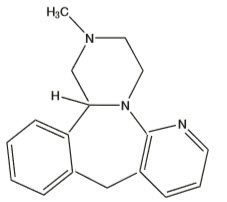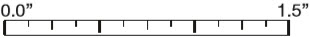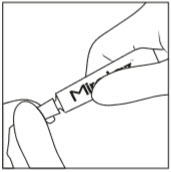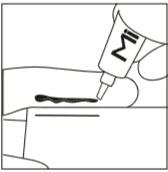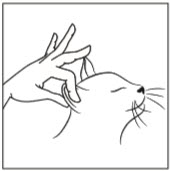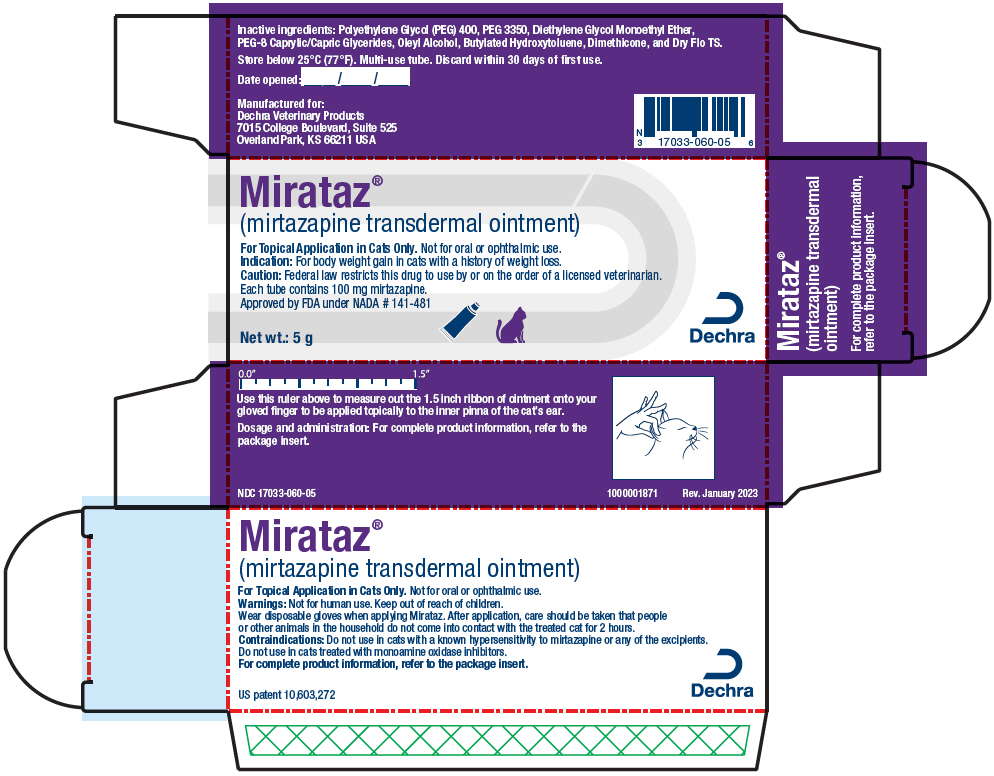 DRUG LABEL: Mirataz
NDC: 17033-060 | Form: OINTMENT
Manufacturer: Dechra Veterinary Products
Category: animal | Type: PRESCRIPTION ANIMAL DRUG LABEL
Date: 20240405

ACTIVE INGREDIENTS: Mirtazapine 20 mg/1 g

Mirataz®
(mirtazapine transdermal ointment)

Each 1 g of Mirataz contains 20 mg mirtazapine (2%). Each 5 g tube contains 100 mg (0.1 g) of mirtazapine.

For topical application in cats only. Not for oral or ophthalmic use.

CAUTION:

Federal law (USA) restricts this drug to use by or on the order of a licensed veterinarian.

DESCRIPTION:

Mirataz (mirtazapine transdermal ointment) is a white to off-white ointment containing 2% (w/w) of mirtazapine suitable for transdermal (topical) administration. Mirataz contains the following inactive ingredients: Polyethylene Glycol (PEG) 400, PEG 3350, Diethylene Glycol Monoethyl Ether, PEG-8 Caprylic/Capric Glycerides, Oleyl Alcohol, Butylated Hydroxytoluene, Dimethicone, and Dry Flo TS.

The structural formula of mirtazapine is:

Molecular Formula: C17H19N3 Molecular Weight: 265.35

VETERINARY INDICATIONS

INDICATION:

Mirataz is indicated for body weight gain in cats with a history of weight loss.

DOSAGE AND ADMINISTRATION:

Administer topically by applying a 1.5-inch ribbon of ointment (approximately 2 mg/cat) on the inner pinna of the cat's ear once daily for 14 days (see Diagrams below).

Wear disposable gloves when applying Mirataz. Dispose of used gloves after each application.

Alternate the daily application of Mirataz between the left and right inner pinna of the ears. Do not administer into the external ear canal. If desired, the inner pinna of the cat's ear may be cleaned by wiping with a dry tissue or cloth immediately prior to the next scheduled dose. If a dose is missed, apply Mirataz the following day and resume daily dosing.

To demonstrate the method of administering the dose, the veterinarian or trained personnel at the clinic should apply the ﬁrst dose in the presence of the owner.

This ruler measures 1.5 inches. Use this ruler to measure the 1.5 inch ribbon of ointment to be applied.

To apply Mirataz:

Step 1: Wear disposable gloves. Twist cap on tube counterclockwise to open.

Step 2: Apply even pressure on tube and squeeze a 1.5-inch line of ointment onto your gloved ﬁnger using the measured line on the carton or in this package insert.

Step 3: Using your gloved ﬁnger, gently rub ribbon of ointment on inside pinna of the cat's ear spreading it evenly over the surface. Dispose of used gloves after each application. If contact with your skin occurs wash thoroughly with soap and warm water.

CONTRAINDICATIONS:

Mirataz is contraindicated in cats with a known hypersensitivity to mirtazapine or to any of the excipients.

Mirataz should not be given in combination, or within 14 days before or after treatment with a monoamine oxidase inhibitor (MAOI) [e.g. selegiline hydrochloride (L-deprenyl), amitraz], as there may be an increased risk of serotonin syndrome.

SAFE HANDLING WARNING

HUMAN WARNINGS:

Not for human use. Keep out of reach of children.

Wear disposable gloves when handling or applying Mirataz to prevent accidental topical exposure.

After application, dispose of used gloves and wash hands with soap and water. After application, care should be taken that people or other animals in the household do not come in contact with the treated cat for 2 hours because mirtazapine can be absorbed transdermally and orally.

However, negligible residues are present at the application site and the body of the cat at 2 hours after dosing.

In case of accidental skin exposure, wash thoroughly with soap and warm water. In case of accidental eye exposure, ﬂush eyes with water. If skin or eye irritation occurs seek medical attention.

In case of accidental ingestion, or if skin or eye irritation occurs, seek medical attention.

PRECAUTIONS:

Do not administer orally or to the eye.

Use with caution in cats with hepatic disease. Mirtazapine may cause elevated serum liver enzymes (See Animal Safety).

Use with caution in cats with kidney disease. Kidney disease may cause reduced clearance of mirtazapine which may result in higher drug exposure.

Upon discontinuation of Mirataz, it is important to monitor the cat's food intake. Food intake may lessen after discontinuation of mirtazapine transdermal ointment. If food intake diminishes dramatically (>75%) for several days, or if the cat stops eating for more than 48 hours, reevaluate the cat.

Mirataz has not been evaluated in cats < 2 kg or less than 6 months of age. The safe use of Mirataz has not been evaluated in cats that are intended for breeding, pregnant, or lactating cats.

ADVERSE REACTIONS:

In a randomized, double-masked, vehicle-controlled ﬁeld study to assess the effectiveness and safety of mirtazapine for the management of weight loss in cats, 115 cats treated with Mirataz and 115 cats treated with vehicle control were evaluated for safety. The vehicle control was an ointment containing the same inert ingredients as Mirataz without mirtazapine. The most common adverse reactions included application site reactions, behavioral abnormalities (vocalization and hyperactivity), and vomiting. The adverse reactions observed in the study and number of cats experiencing each adverse reaction is summarized in Table 1 below.

Table 1. Adverse Reactions Reported During the Field Study
Adverse Reaction | Mirataz N=115 (%) | Vehicle Control N=115 (%)
Application site (Ear pinna)
Erythema | 12 (10.4%) | 20 (17.4%)
Crust/Scab | 3 (2.6%) | 6 (5.2%)
Residue | 3 (2.6%) | 8 (7.0%)
Scaling/Dryness | 3 (2.6%) | 3 (2.6%)
Dermatitis or irritation | 1 (0.9%) | 9 (7.8%)
Alopecia | 1 (0.9%) | 2 (1.7%)
Pruritus | 1 (0.9%) | 4 (3.5%)
Behavioral
Vocalization | 13 (11.3%) | 2 (1.7%)
Hyperactivity | 8 (7.0%) | 1 (0.9%)
Disoriented state or ataxia | 4 (3.5%) | 2 (1.7%)
Lethargy/weakness | 4 (3.5%) | 9 (7.8%)
Attention Seeking | 3 (2.6%) | 0
Aggression | 2 (1.7%) | 0
Physical Examination or Observational
Vomiting | 13 (11.3%) | 15 (13.0%)
Dehydration | 6 (5.2%) | 5 (4.3%)
Diarrhea or soft stool | 6 (5.2%) | 7 (6.1%)
Heart murmur | 5 (4.3%) | 7 (6.1%)
Inappetence | 5 (4.3%) | 5 (4.3%)
Renal insufﬁciency [One cat with renal insufﬁciency was reported with a serious adverse reaction of acute renal failure, hematuria, and pyuria at the Week 2 visit. The cat was enrolled with a history of chronic kidney disease. Euthanasia was elected and necropsy revealed hypertrophic cardiomyopathy, bilateral parathyroid hyperplasia, and mild to moderate renal disease.] | 4 (3.5%) | 0
Ear infection | 3 (2.6%) | 0
Urinary tract infection | 3 (2.6%) | 0
Clinical Pathology
Hematuria | 7 (6.1%) | 1 (0.9%)
Elevated BUN (without creatinine) [At Week 2, blood urea nitrogen (BUN) values were signiﬁcantly higher in the Mirataz group compared to the vehicle control group (p<0.10). The BUN in the Mirataz group was 43.60 mg/dL (reference range 16-37 mg/dL) compared to 36.05 mg/dL in the vehicle control group.] | 6 (5.2%) | 0
Elevated creatinine and BUN | 5 (4.3%) | 1 (0.9%)
Hyperphosphatemia | 5 (4.3%) | 0
Hypokalemia | 5 (4.3%) | 2 (1.7%)
Pyuria | 5 (4.3%) | 0
Anemia | 3 (2.6%) | 8 (7.0%)
Low urine speciﬁc gravity | 3 (2.6%) | 1 (0.9%)
Monocytosis | 3 (2.6%) | 2 (1.7%)
Neutrophilia | 3 (2.6%) | 2 (1.7%)

Post study, follow-up was done in 199 cats (103 in the Mirataz (mirtazapine transdermal ointment) group and 96 in the vehicle control group).

Following cessation of Mirataz, four cats were reported as being less social or less restless, one cat was reported as more active, and one cat was reported with increased hissing and urinating out of the litter box.

To report suspected adverse events, for technical assistance or to obtain a copy of the SDS, contact Dechra at (866) 933-2472.

For additional information about adverse drug experience reporting for animal drugs, contact FDA at 1-888-FDA-VETS or online at http://www.fda.gov/reportanimalae

INFORMATION FOR CAT OWNERS:

Upon discontinuation of Mirataz, it is important to monitor your cat's food intake. Your cat's food intake may lessen after discontinuation of mirtazapine transdermal ointment. If food intake diminishes dramatically (>75%) for several days or if your cat stops eating for more than 48 hours, contact your veterinarian.

CLINICAL PHARMACOLOGY:

Mechanism of Action:

The exact mechanism by which mirtazapine induces weight gain has not been clearly elucidated but appears to be multifactorial.^1 Mirtazapine is an α2-adrenergic receptor antagonist nor-adrenergic and serotonergic antidepressant drug. Mirtazapine is known to be a potent antagonist of 5-HT2 and 5-HT3 serotonin receptors in the central nervous system (CNS), and a potent inhibitor of histamine H1 receptors. Because mirtazapine blocks 5-HT2 and 5-HT3 receptors, only 5-HT1A- mediated serotonergic transmission is enhanced. Inhibition of 5-HT2 receptors may account for the orexigenic effects of mirtazapine. Another hypothesis is that mirtazapine induced weight gain may be secondary to changes in leptin and the tumor necrosis factor α(TNF-α) cytokine system.^2 A study by Fernstorm (1995) demonstrated a reduction of the basal metabolic rate in patients treated with antidepressants in general.^3

Pharmacokinetics:

In a crossover study in eight cats to determine the relative bioavailability of oral and transdermal 2% mirtazapine, the mean half-life (26.8 hours) with topical administration was over 2× longer than the mean half-life (10.1 hours) with oral administration.

The doses used in the target animal safety study were higher (2.8 to 5.4 mg) than the label dose. Based on dose proportionality in AUC0-24hr and Cmax observed in this study, these pharmacokinetic parameters were extrapolated for the 2 mg/cat label dose administered once per day for 35 days (see Table 2).

Steady state was achieved within 14 days. The median accumulation between ﬁrst and 35th dose was 3.71× (based on AUC ratio) and 3.90× (based on Cmax ratio).

Table 2. Plasma pharmacokinetic parameters at steady state after 2 mg/cat dose of mirtazapine 2.0% transdermal ointment in healthy cats
Parameter | Unit | Mean (SD)
Cmax | ng/mL | 32.1 (19.9)
Tmax | hr | 6 (2-6) [Tmax = time to maximum plasma concentration (reported as median and range)]
AUC0-24hr | hr*ng/mL | 410.3 (213.5)
Half-life [The half-life value is reﬂective of both topical and oral exposure. In another study where cats wore Elizabethan collar to restrict access to their ears and consequent oral exposure, a longer half-life (Mean= 20.7 hr) was observed.] | hr | 11.2 (2.98)
Cmax = extrapolated maximum plasma concentration
AUC0-24hr = extrapolated area under the plasma time vs. concentration curve

EFFECTIVENESS:

The effectiveness of Mirataz (mirtazapine transdermal ointment) was demonstrated in a randomized, double-masked, vehicle-controlled, multi-site ﬁeld study involving client-owned cats of various breeds.

Enrolled cats were ≥ 1 year of age and had existing documented medical history of ≥ 5% weight loss deemed clinically signiﬁcant. The most common pre-existing conditions included renal insufﬁciency, vomiting, and hyperthyroidism.

Some cats had more than one pre-existing condition. Cats were randomized to treatment groups in a 1:1 ratio of Mirataz to vehicle control. A total of 230 cats were enrolled and received either Mirataz (115 cats) or a vehicle control (115 cats) containing the same inert ingredients without mirtazapine. The cats were 2.8-24.6 years of age and weighed 2.1-9.2 kg. The dosage was a 1.5-inch ribbon (approximately 2 mg/cat) mirtazapine or vehicle ointment administered topically to the inner pinna of the cat's ear.

A total of 177 cats were determined to be eligible for the effectiveness analysis; 83 cats were in the Mirataz group and 94 cats were in the vehicle control group. The primary effectiveness endpoint was the mean percent change in body weight from Day 1 to the Week 2 Visit.

At Week 2, the mean percent increase in body weight from Day 1 was 3.94% in the mirtazapine group and 0.41% in the vehicle control group. The difference between the two groups was signiﬁcant (p<0.0001) based on a two-sample t-test assuming equal variances. A 95% conﬁdence interval on the mean percent change in body weight for the Mirataz group is (2.77, 5.11), demonstrating that the mean percent change is statistically different from and greater than 0.

ANIMAL SAFETY:

The margin of safety of mirtazapine was evaluated in one laboratory study, a comprehensive review of six pilot studies (ﬁve laboratory and one clinical) utilizing the ﬁnal market formulation, and one laboratory study that was not ﬁnal market formulation.

Laboratory Safety Study:

In a 6-week laboratory safety study, 48 healthy cats aged 7-10 months were dosed topically with mirtazapine once daily at 0 mg/kg (vehicle control), 1.1 mg/kg (1.4 to 2.7×), 3.2 mg/kg (4.3-7.5×), and 5.3 mg/kg (7.1-12.2×) body weight.

Four cats/sex/group in the 1.1 and 3.2 mg/kg groups were dosed topically to the inner pinna of the ear, alternating between right and left ears.

Eight cats/sex/group in the 0 and 5.3 mg/kg groups were dosed topically to the inner pinna of the ear, splitting the dose between both ears. Four cats/sex/group in the 0 and 5.3 mg/kg groups were maintained and monitored during a 4-week recovery period.

6 Week Dosing Period

Application of mirtazapine and vehicle control was associated with ear ﬂicking, head shaking, pulling away/ﬂinching and infrequently with struggling/fractious behavior, and hypersalivation. Inner and outer pinna erythema, ﬂaking, alopecia, and thickening were observed in all cats in all groups. Erythema, crusting, alopecia, and scabbing of the skin, mostly around the head and neck, was frequently observed in all groups and occasionally affected the tail, tarsi or carpi, likely due to spread of the ointment to these areas by self-grooming.

Mirtazapine administration resulted in increased vocalization, hyperactivity, attention-seeking behaviors, and tremors in all mirtazapine dose groups. Frank blood in the stool was infrequently observed in the vehicle control, 3.2, and 5.3 mg/kg groups. Polyuria was observed in all groups. Polydipsia was observed in one cat in the 5.3 mg/kg group. Three cats (one from each mirtazapine dose group) were isosthenuric. Eight cats developed cystitis with or without urethral obstruction throughout the study in all groups. One cat each from the vehicle control and 3.2 mg/kg group were euthanized early on Day 35 due to urethral obstruction.

Two cats from the 1.1 mg/kg group had either ventricular premature contractions (VPC) or tall R waves, and one cat from the 5.3 mg/kg group had both VPC and a right axis deviation.

Eosinophilia was noted sporadically in the vehicle control, 1.1, and 5.3 mg/kg groups. Mild elevations in ALT values were noted sporadically in vehicle control, 3.2, and 5.3 mg/kg groups.

On Day 15, one cat in the 3.2 mg/kg group demonstrated a marked ALT elevation of 3397 U/L, with concurrent elevations in AST and GGT. By Day 42, the ALT declined to 109 U/L and the AST and GGT returned to within normal limits.

Gross pathology ﬁndings, conﬁrmed with histopathology, were hyperplastic dermatitis (alopecia, hyperkeratosis, thickening, and ceruminous gland secretion) of the pinnae in all cats and ﬁndings consistent with cystitis (mucosal urinary bladder hemorrhage, mottled-dark red appearance, and irregular contour) in four male cats (two vehicle control, one 3.2 mg/kg and one 5.3 mg/kg). Additional histopathologic ﬁndings included pyelonephritis (two vehicle control and one 5.3 mg/kg), nephrocalcinosis (three vehicle control, one 1.1 mg/kg, three 3.2 mg/kg, and one 5.3 mg/kg), necrosis of the kidneys (one vehicle control and one 3.2 mg/kg), unilateral hypoplasia of the thyroid gland (two 5.3 mg/kg), and unilateral hypertrophy of the thyroid gland (one 5.3 mg/kg).

4 Week Recovery Period

Following a 4-week recovery period, ALT elevations resolved. Polyuria was reduced and only occurred in two cats in the 5.3 mg/kg group. Pinnal lesions (erythema and ﬂaking) completely resolved in the vehicle control and improved in the 5.3 mg/kg groups. Ear thickening improved in both groups.

Pilot Safety Studies:

In six pilot studies (ﬁve laboratory and one clinical study) utilizing the ﬁnal market formulation of Mirataz, and one laboratory study that utilized non-ﬁnal market formulation, a total of 76 cats were administered mirtazapine. Five studies administered mirtazapine ointment topically (0.5-5.3 mg/kg), one study administered mirtazapine topically and orally (0.5 mg/kg), and one study administered mirtazapine orally (10.6 mg/cat).

The most common observations were ear pinnae reactions (erythema with or without blood and ﬂaking), mild behavioral observations (vocalization and tremors), vomiting, and diarrhea.

One study reported six cats with blood in the stool. Two studies reported one cat each showing aggression. One study reported polyuria in one cat; another study reported stranguria and possible urinary tract infection in one cat. Two studies reported cardiac abnormalities, including sinus tachycardia not present at baseline, development of a grade 3/6 heart murmur, tall QRS complexes, and left or right axis deviation. One study reported one cat with ataxia. In the studies that administered mirtazapine orally, salivation and lip licking were frequently observed.

In the terminal study administering 5.3 mg/kg mirtazapine topically, histopathology showed chronic hyperplastic dermatitis at the application site.

STORAGE:

Store below 25°C (77°F). Multi-use tube. Discard within 30 days of ﬁrst use.

HOW SUPPLIED:

Mirataz is supplied in a 5 gram aluminum tube.
NDC 17033-060-05

REFERENCES:

1. Laimer, M., Kramer-Reinstadler, K., Rauchenzauner, M., Lechner-Schoner, T., Strauss, R., Engl, J., & Ebenbichler, C. F. (2006). Effect of mirtazapine treatment on body composition and metabolism. The Journal of clinical psychiatry, 67(3), 421-424.
2. Kraus, T., Haack, M., Schuld, A., Hinze-Selch, D., Koethe, D., & Pollmächer, T. (2002). Body weight, the tumor necrosis factor system, and leptin production during treatment with mirtazapine or venlafaxine. Pharmacopsychiatry, 35(06), 220-225.
3. Fernstrom, M. H. (1995). Drugs that cause weight gain. Obesity research, 3(S4), 435S-439S.

Approved by FDA under NADA # 141-481

Manufactured for:
Dechra Veterinary Products, 7015 College Boulevard
Suite 525, Overland Park, KS 66211 USA

US Patent 10,603,272

Mirataz® is a registered trademark of Dechra Limited.

1000001870
Rev. January 2024

PRINCIPAL DISPLAY PANEL - 5 g Tube Carton

Mirataz®
(mirtazapine transdermal ointment)

For Topical Application in Cats Only. Not for oral or ophthalmic use.
Indication: For body weight gain in cats with a history of weight loss.
Caution: Federal law restricts this drug to use by or on the order of a licensed veterinarian.
Each tube contains 100 mg mirtazapine.
Approved by FDA under NADA # 141-481

Net wt.: 5 g

Dechra